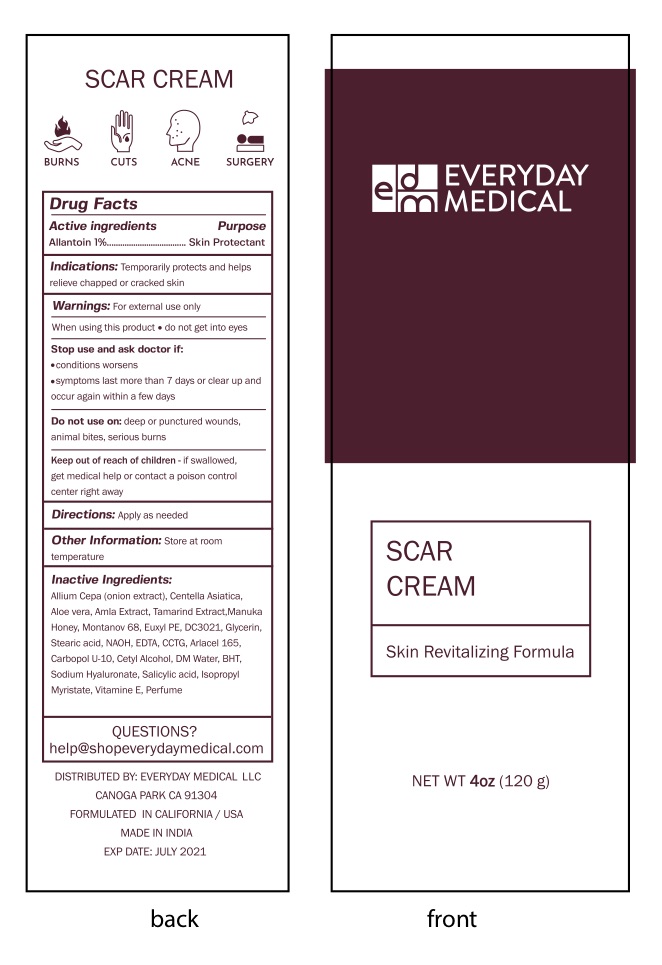 DRUG LABEL: Scar Cream
NDC: 72982-1905 | Form: CREAM
Manufacturer: Everyday Medical LLC
Category: otc | Type: HUMAN OTC DRUG LABEL
Date: 20190712

ACTIVE INGREDIENTS: ALLANTOIN 1 g/100 g
INACTIVE INGREDIENTS: CETOSTEARYL ALCOHOL; CETEARYL GLUCOSIDE; CYCLOMETHICONE 5; PHENYL TRIMETHICONE; ALKYL (C12-15) BENZOATE; CARBOMER INTERPOLYMER TYPE A (55000 CPS); WATER; CLOVE OIL; ALOE VERA LEAF; CETYL ALCOHOL; ONION; GLYCERIN; STEARIC ACID; EDETIC ACID; GLYCERYL STEARATE/PEG-100 STEARATE; MELALEUCA ALTERNIFOLIA LEAF; BUTYLATED HYDROXYTOLUENE; SODIUM HYDROXIDE; CAPRYLIC/CAPRIC/LAURIC TRIGLYCERIDE; PHYLLANTHUS EMBLICA WHOLE; TAMARIND; CENTELLA ASIATICA

Scar Cream

Active Ingredients

Allantoin 1% Skin Protectant

PURPOSE

Skin protectant

INDICATIONS AND USAGE

temporarily protects and helps relieve chapped or cracked skin

Warnings

For external use only

Do not get into eyes

Stop use and ask a doctor if

- condition worsens
- Symptoms last more than 7 days or clear up and occur again within a few days

Do not use on deep or punctured wounds, animal bites, serious burns

Keep out of reach of children. If swallowed get medical help or contact a Poison Control Center right away

DOSAGE AND ADMINISTRATION

Apply as needed

INACTIVE INGREDIENT

CENTELLA ASIATICA

CYCLOMETHICONE 5
PHENYL TRIMETHICONE
ALKYL (C12-15) BENZOATE
CARBOMER INTERPOLYMER TYPE A (55000 CPS)
WATER
CLOVE OIL
ALOE VERA LEAF
CETYL ALCOHOL
ONION
GLYCERIN
STEARIC ACID
EDETIC ACID
GLYCERYL STEARATE/PEG-100 STEARATE
MELALEUCA ALTERNIFOLIA LEAF
BUTYLATED HYDROXYTOLUENE
SODIUM HYDROXIDE
CAPRYLIC/CAPRIC/LAURIC TRIGLYCERIDE
PHYLLANTHUS EMBLICA WHOLE
TAMARIND
CETOSTEARYL ALCOHOL

CETEARYL GLUCOSIDE